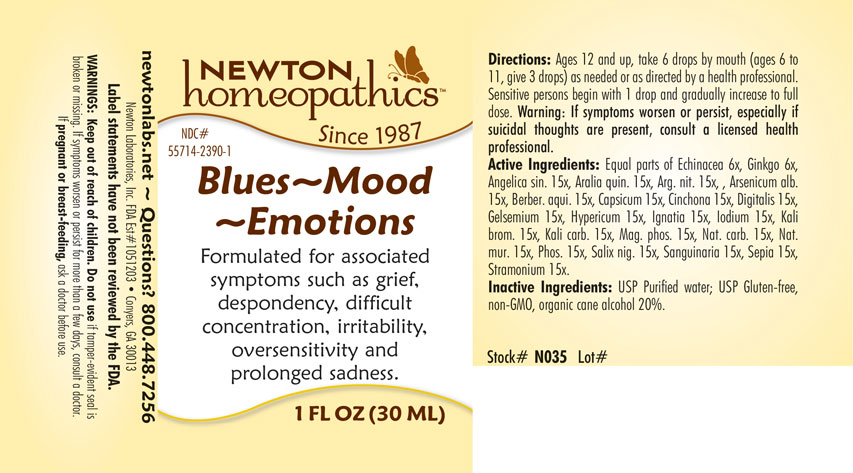 DRUG LABEL: Blues - Mood - Emotions
NDC: 55714-2390 | Form: LIQUID
Manufacturer: Newton Laboratories, Inc.
Category: homeopathic | Type: HUMAN OTC DRUG LABEL
Date: 20201124

ACTIVE INGREDIENTS: ECHINACEA, UNSPECIFIED 6 [hp_X]/1 mL; GINKGO 6 [hp_X]/1 mL; MAHONIA AQUIFOLIUM ROOT BARK 15 [hp_X]/1 mL; ANGELICA SINENSIS ROOT 15 [hp_X]/1 mL; AMERICAN GINSENG 15 [hp_X]/1 mL; SILVER NITRATE 15 [hp_X]/1 mL; ARSENIC TRIOXIDE 15 [hp_X]/1 mL; CAPSICUM 15 [hp_X]/1 mL; CINCHONA OFFICINALIS BARK 15 [hp_X]/1 mL; DIGITALIS 15 [hp_X]/1 mL; GELSEMIUM SEMPERVIRENS ROOT 15 [hp_X]/1 mL; HYPERICUM PERFORATUM 15 [hp_X]/1 mL; STRYCHNOS IGNATII SEED 15 [hp_X]/1 mL; IODINE 15 [hp_X]/1 mL; POTASSIUM BROMIDE 15 [hp_X]/1 mL; POTASSIUM CARBONATE 15 [hp_X]/1 mL; MAGNESIUM PHOSPHATE, DIBASIC TRIHYDRATE 15 [hp_X]/1 mL; SODIUM CARBONATE 15 [hp_X]/1 mL; SODIUM CHLORIDE 15 [hp_X]/1 mL; PHOSPHORUS 15 [hp_X]/1 mL; SALIX NIGRA BARK 15 [hp_X]/1 mL; SANGUINARIA CANADENSIS ROOT 15 [hp_X]/1 mL; SEPIA OFFICINALIS JUICE 15 [hp_X]/1 mL; DATURA STRAMONIUM 15 [hp_X]/1 mL
INACTIVE INGREDIENTS: WATER; ALCOHOL

Blues 2390L

OTC - PREGNANCY OR BREAST FEEDING SECTION

If pregnant or brest-feeding, ask a doctor before use.

INDICATIONS & USAGE SECTION

Formulated for associated symptoms such as grief, despondency, difficult concentration, irritability, oversensitivity and prolonged sadness.

DOSAGE & ADMINISTRATION SECTION

Directions: Ages 12 and up, take 6 drops by mouth (ages 6 to 11, give 3 drops) as needed or as directed by a health professional. Sensitive persons begin with 1 drop and gradually increase to full dose. Warning: If symptoms worsen or persist, especially if suicidal thouhts are present, consult a licensed health professional.

OTC - ACTIVE INGREDIENT SECTION

Equal parts of Echinacea 6x, Ginkgo 6x, Angelica sin. 15x, Aralia quin. 15x, Arg. nit. 15x, Arsenicum alb. 15x, Berber. aqui. 15x, Capsicum 15x, Cinchona 15x, Digitalis 15x, Gelsemium 15x, Hypericum 15x, Ignatia 15x, Iodium 15x, Kali brom. 15x, Kali carb. 15x, Mag. phos. 15x, Nat. carb. 15x, Nat. mur. 15x, Phos. 15x, Salix nigra 15x, Sanguinaria 15x, Sepia 15x, Stramonium 15x.

OTC - PURPOSE SECTION

Formulated for associated symptoms such as grief, despondency, difficult concentration, irritability, oversensitivity and prolonged sadness.

INACTIVE INGREDIENT SECTION

Inactive Ingredients: USP Purified Water; USP Gluten-free, non-GMO, organic cane alcohol 20%.

OTC - KEEP OUT OF REACH OF CHILDREN SECTION

Keep out of reach of children.

QUESTIONS SECTION

newtonlabs.net ~ Questions? 800.448.7256

Newton Laboratories, Inc. FDA Est # 1051203 - Conyers, GA 30013

WARNINGS SECTION

WARNINGS: Keep out of reach of children. Do not use if tamper-evident seal is missing or broken. If symptoms persist for more than a few days, consult a doctor. If pregnant or breat-feeding, ask a doctor before use.